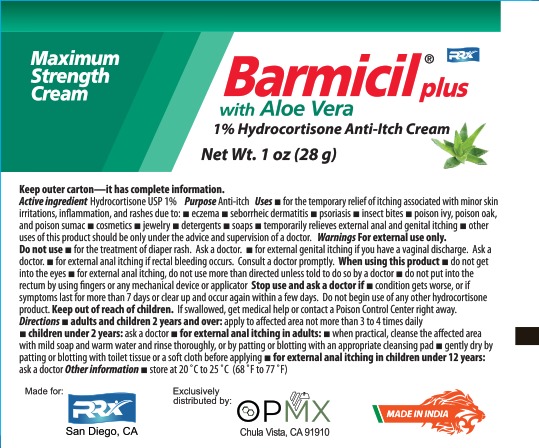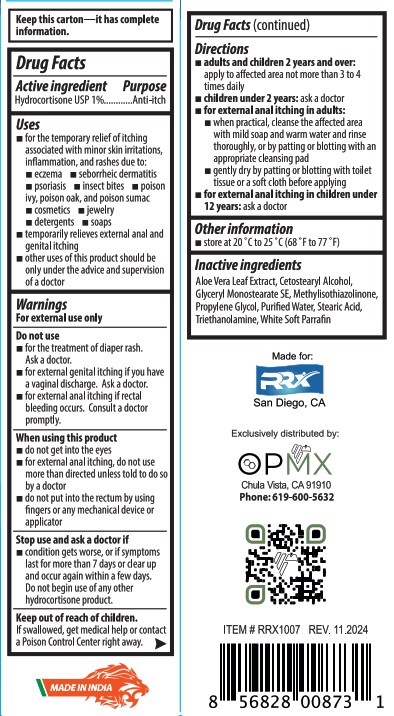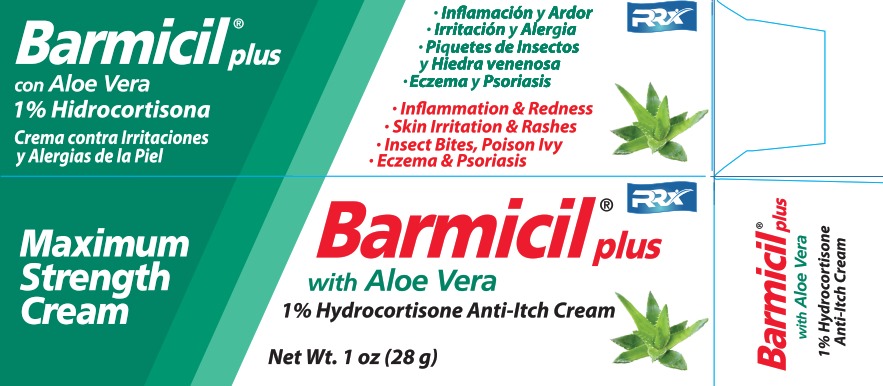 DRUG LABEL: Barmicil Anti-itch
NDC: 69729-301 | Form: CREAM
Manufacturer: OPMX LLC
Category: otc | Type: HUMAN OTC DRUG LABEL
Date: 20241128

ACTIVE INGREDIENTS: HYDROCORTISONE 1 g/100 g
INACTIVE INGREDIENTS: POTASSIUM SORBATE; LIGHT MINERAL OIL; SODIUM CETOSTEARYL SULFATE; WHITE PETROLATUM; WHITE WAX; ALOE VERA LEAF; CETOSTEARYL ALCOHOL; WATER; SODIUM BENZOATE; SODIUM LAURYL SULFATE; GLYCERIN

Barmicil Plus

Active Ingredient

Hydrocortisone 1 %

Purpose

Anti-Itch

Uses

for the temporary relief of itching associated with minor skin irritations, inflammation, and rashes due to:

eczema

seborrheic dermatitis

psoriasis

insect bites

poison ivy, poison oak, and poison sumac

cosmetics

jewelry

detergents

soaps

temporarily relieves external anal and genital itching

other uses of this product should be only under the advice and supervision of a doctor

Warnings

For external use only

Do not use

for the treatment of diaper rash. Ask a doctor.

for external genital itching if you have a vaginal discharge. Ask a doctor.

for external anal itching if rectal bleeding occurs. Consult a doctor promptly.

When using this product

do not get into the eyes

for external anal itching, do not use more than directed unless told to do so by a doctor

do not put into the rectum by using fingers or any mechanical device or applicator

Stop us and ask doctor if

condition gets worse, or if symptoms last for more than 7 days or clear up and occur again within a few days. Do not begin use of any other hydrocortisone product.

Keep out of reach of children

If swallowed, get medical help or contact a Poison Control Center right away.

Directions

adults and children 2 years and over: apply to affected area not more than 3 to 4 times daily

children under 2 years: ask a doctor

for external anal itching in adults:

when practical, cleanse the affected area with mild soap and warm water and rinse thoroughly, or by patting or blotting with an appropriate cleansing pad.

gently dry by patting or blotting with toilet tissue or a soft cloth before applying.

for external anal itching in children under 12 years: ask a doctor

Other information

store at 20 °C to 25 °C (68 °F to 77 °F)

Inactive ingredient

Aloe Vera Leaf Extract, cetearyl alcohol, glycerin, light mineral oil, potassium sorbate, purified water, sodium benzoate, sodium cetearyl sulfate, sodium lauryl sulfate, white petrolatum, white wax.

Questions?

call 619-600-5632

Label

Barmicil ® plus

with Aloe Vera

1% Hydrocortisone Anti-Itch Cream

Net Wt. 1 0z (28g)

Maximum Strenght Cream

- Inflammation & Redness
- Skin Irritation & Rashes
- Insect Bites, Poison Ivy
- Eczema & Psoriasis

Made for RRX

San Diego, CA

Exclusively distributed by:

OPMX

Chula Vista, CA 91910

Phone: 619-600-5632